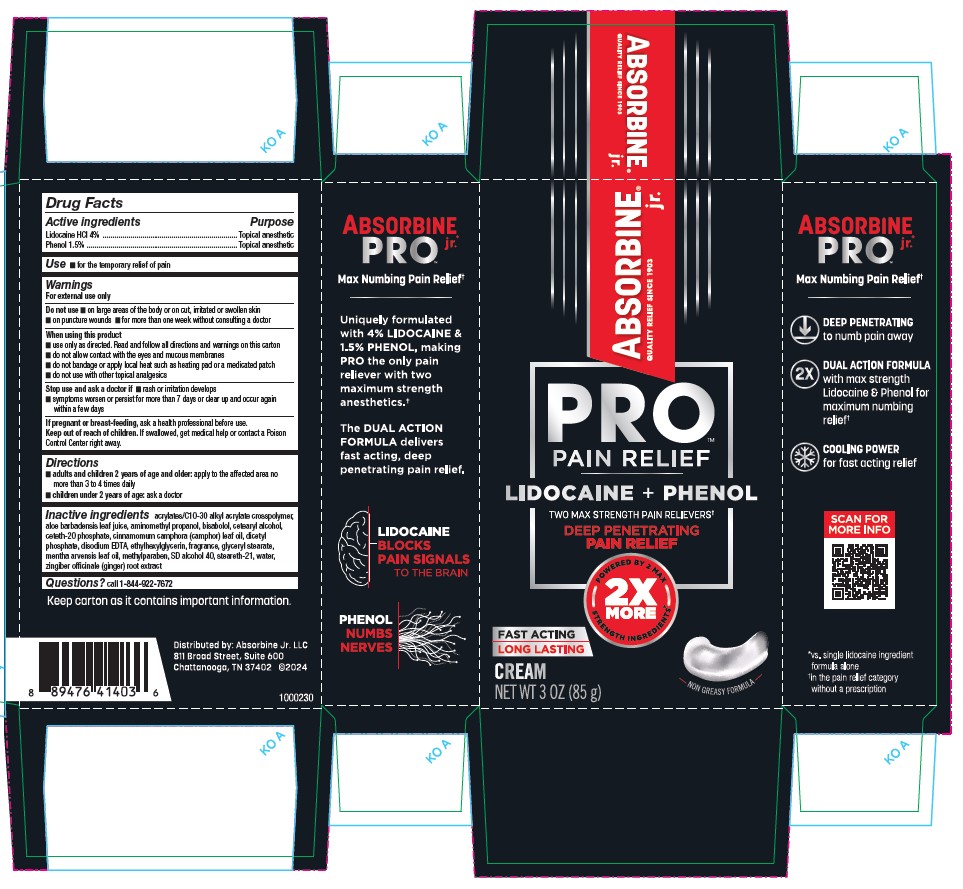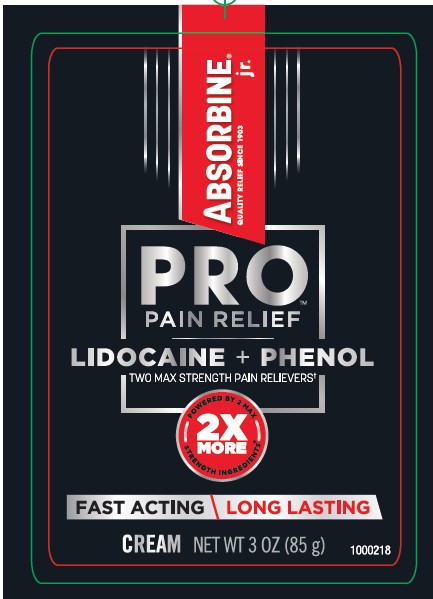 DRUG LABEL: Absorbine Jr Pro Cream
NDC: 69693-418 | Form: CREAM
Manufacturer: Clarion Brands, LLC
Category: otc | Type: HUMAN OTC DRUG LABEL
Date: 20251223

ACTIVE INGREDIENTS: LIDOCAINE 40 mg/1 g; PHENOL 15 mg/1 g
INACTIVE INGREDIENTS: CARBOMER COPOLYMER TYPE A (ALLYL PENTAERYTHRITOL CROSSLINKED); ALOE ARBORESCENS LEAF; AMINOMETHYLPROPANOL; LEVOMENOL; CETOSTEARYL ALCOHOL; CETETH-20 PHOSPHATE; CAMPHOR LEAF OIL; DIHEXADECYL PHOSPHATE; EDETATE DISODIUM ANHYDROUS; ETHYLHEXYLGLYCERIN; GLYCERYL MONOSTEARATE; MENTHA ARVENSIS LEAF OIL; METHYLPARABEN; ALCOHOL; STEARETH-21; WATER; GINGER

Absorbine Jr Pro Cream
Drug Facts

Active ingredients | Purpose
Lidocaine HCl 4% | Topical anesthetic
Phenol 1.5% | Topical anesthetic

Use

- for the temporary relief of pain

Warnings

For external use only.

Do not use

- on large areas of the body or on cut, irritated or swollen skin
- on puncture wounds
- for more than one week without consulting a doctor.

When using this product

- use only as directed. Read and follow all directions and warnings on this carton
- do not allow contact with the eyes and mucous membranes
- do not bandage or apply local heat such as heating pad or a medicated patch
- do not use with other topical analgesics.

Stop use and ask a doctor if

- rash or irritation develops
- symptoms worsen or persist for more than 7 days or clear up and occur again within a few days.

PREGNANCY OR BREAST FEEDING

If pregnant or breast-feeding, ask a health professional before use.

Keep out of reach of children.If swallowed, get medical help or contact a Poison Control Center right away.

Directions

- adults and children 2 years of age and older:apply to the affected area no more than 3 to 4 times daily
- children under 2 years of age;: ask a doctor

Inactive Ingredients

Acrylates/C10-30 alkyl acrylate crosspolymer, Aloe barbadensis leaf juice, Aminomethyl propanol, Bisabolol, Cetearyl alcohol, Ceteth-20 phosphate, Cinnamomum camphora (camphor) leaf oil, Dicetyl phosphate, Disodium EDTA, Ethylhexylglycerin, Fragrance, Glyceryl stearate, Mentha arvensis leaf oil, Methylparaben, SD alcohol 40, Steareth-21, Water, Zingiber officinale (ginger) root extract

Questions?call 1-844-7675

Principal Display Panel

ABSORBINE jr.
QUAITY RELIEF SINCE 1903
PRO™
PAIN RELIEF
LIDOCAIN + PHENOL
TWO MAX STRENGTH PAIN RELIERS†
DEEP PENETRATING
PAIN RELIEF
2X
MORE
POWERED BY 2 MAX
STRENGTH INGREDIENTS*
NON GREASY FORMULA
FAST ACTING
LONG LASTING
CREAM
NET WT 3 OZ (985g)
ABSORBINE
PRO JR.
Max Numbing Pain Relief†
Uniquely Formulated
with 4% LIDOCAINE &
1.5& PHENOL , making
PRO the only pain
reliever with two
maximum strength
anesthetics.†
THE DUEL ACTION
FORMULA delivers
fast acting, deep
Penetrating pain relief.
LIDOCAINE
BLOCKS
PAIN SIGNALS
TO THE BRAIN
PHENOL
NUMBS
NERVES
ABSORBINE
PRO JR®
Max Numbing Pain Relief†
DEEP PENETRATING
to numb pain away
2X DUAL ACTION FORMULA
with max strength
Lidocaine & Phenol for
maximum numbing
relief †
COOLING POWER
for fast acting relief
*vs. single lidocaine ingredient
formula alone
†without a prescription

Keep carton as it contains important information.
Distributed by: Absorbine Jr. LLC
811 Broad Street, Suite 600
Chattanooga, TN 37402 @2024
*vs. Single Lidocaine Ingredient Formula Alone
Child resistant packaging. Replace cap after each use.
1000230

ABBORBINE jr.
QUAITY RELIEF SINCE 1903
PRO™
PAIN RELIEF
LIDOCAINE + PHENOL
TWO MAX STRENGTH PAIN RELIEVERS†
2X
MORE
POWERED BY 2 MAX STRENGTH INGREDIENTS®
FAST ACTING \ LONG LASTING
CREAMNET WT 3 OZ (85 G)
18000218